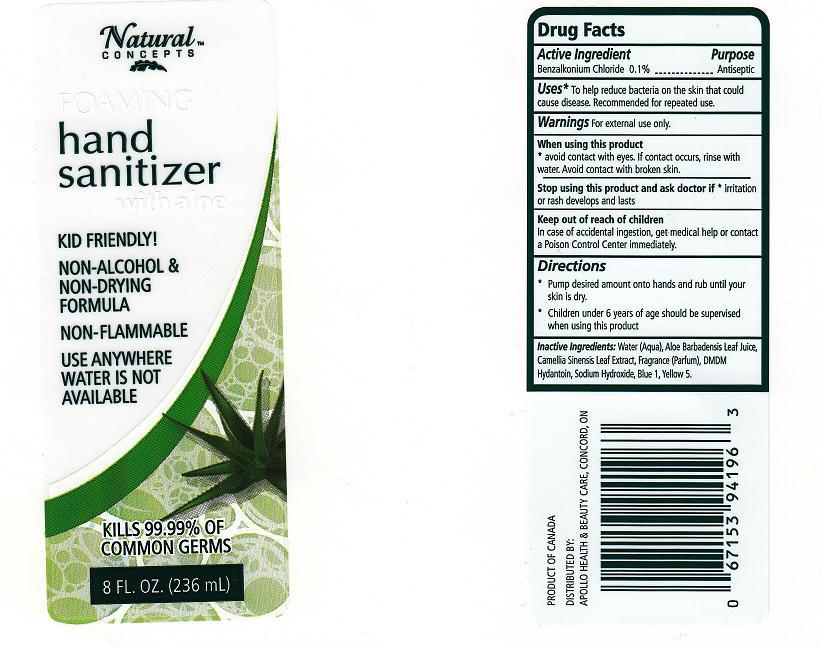 DRUG LABEL: FOAMING HAND SANITIZER
NDC: 63148-240 | Form: LIQUID
Manufacturer: APOLLO HEALTH AND BEAUTY CARE
Category: otc | Type: HUMAN OTC DRUG LABEL
Date: 20100625

ACTIVE INGREDIENTS: BENZALKONIUM CHLORIDE 0.1000 mL/100 mL

DRUG FACTS BOX (BACK LABEL)

ACTIVE INGREDIENT

BENZALKONIUM CHLORIDE 0.1% (ANTISEPTIC)

USES AND DIRECTIONS

- USES: TO HELP REDUCE BACTERIA ON THE SKIN THAT COULD CAUSE DISEASE. RECOMMENDED FOR REPEATED USE.
- DIRECTIONS: PUMP DESIRED AMOUNT ONTO HANDS AND RUB UNTIL YOUR SKIN IS DRY. CHILDREN UNDER 6 YEARS OF AGE SHOULD BE SUPERVISED WHEN USING THIS PRODUCT.

WARNINGS

- FOR EXTERNAL USE ONLY.

WHEN USING THIS PRODUCT

- AVOID CONTACT WITH EYES. IF CONTACT OCCURS, RINSE WITH WATER. AVOID CONTACT WITH BROKEN SKIN.

STOP USE AND ASK A DOCTOR IF

- SKIN IRRITATION OR REDNESS DEVELOPS AND LASTS.

KEEP OUT OF REACH OF CHILDREN

- IN CASE OF ACCIDENTAL INGESTION, GET MEDICAL HELP OR CONTACT A POISON CONTROL CENTER IMMEDIATELY.

PACKAGE FRONT AND BACK LABELS

- 8OZ FRONT AND BACK LABELS: nc08.jpg